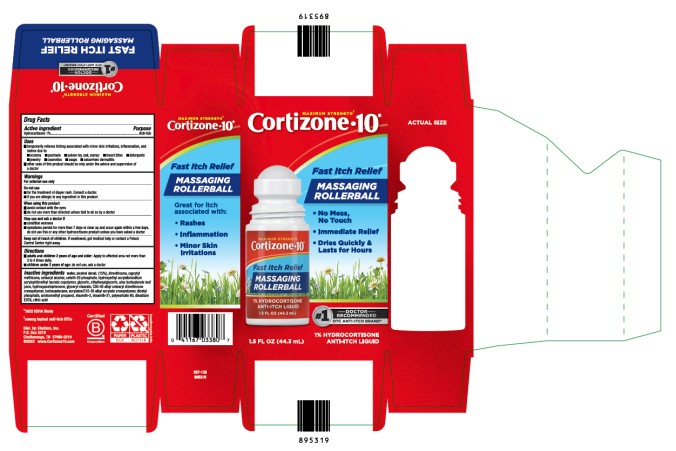 DRUG LABEL: Cortizone 10 Itch Relief Massaging Rollerball
NDC: 41167-0338 | Form: CREAM
Manufacturer: Chattem, Inc.
Category: otc | Type: HUMAN OTC DRUG LABEL
Date: 20240501

ACTIVE INGREDIENTS: HYDROCORTISONE 1 g/100 g
INACTIVE INGREDIENTS: WATER; ALCOHOL; DIMETHICONE; CAPRYLYL TRISILOXANE; CETOSTEARYL ALCOHOL; CETETH-20 PHOSPHATE; HYDROXYETHYL ACRYLATE/SODIUM ACRYLOYLDIMETHYL TAURATE COPOLYMER (100000 MPA.S AT 1.5%); GLYCERIN; ETHYLHEXYLGLYCERIN; ALOE VERA LEAF; HYDROXYACETOPHENONE; GLYCERYL MONOSTEARATE; C30-45 ALKYL CETEARYL DIMETHICONE CROSSPOLYMER; ISOHEXADECANE; DIHEXADECYL PHOSPHATE; AMINOMETHYLPROPANOL; STEARETH-2; STEARETH-21; POLYSORBATE 60; EDETATE DISODIUM ANHYDROUS; CITRIC ACID MONOHYDRATE; CARBOMER COPOLYMER TYPE A

Cortizone 10 Itch Relief Massaging Rollerball

Cortizone 10 Itch Relief Massaging Rollerball

Drug Facts

Purpose

Hydrocortisone 1%...........................................................................................................................................Anti-itch

Uses

■ temporarily relieves itching associated with minor skin irritations, inflammation, and rashes due to:

■ eczema ■ psoriasis ■ poison ivy, oak, sumac ■ insect bites ■ detergents ■ jewelry ■ cosmetics

■ soaps ■ seborrheic dermatitis

■ other uses of this product should be only under the advice and supervision of a doctor

Warnings

For external use only

Do not use

■ for the treatment of diaper rash. Consult a doctor.

■ if you are allergic to any ingredient in this product

When using this product

■ avoid contact with the eyes ■ do not use more than directed unless told to do so by a doctor

Stop use and ask a doctor if

■ condition worsens

■ symptoms persist for more than 7 days or clear up and occur again within a few days, do not use this or any other hydrocortisone product unless you have asked a doctor

Keep out of reach of children.

If swallowed, get medical help or contact a Poison Control Center right away.

Directions

■ adults and children 2 years of age and older: Apply to affected area not more than 3 to 4 times daily.

■ children under 2 years of age: do not use, ask a doctor

Inactive ingredients

water, alcohol denat. (15%), dimethicone, caprylyl methicone, cetearyl alcohol, ceteth-20 phosphate, hydroxyethyl acrylate/sodium acryloyldimethyl taurate copolymer, glycerin, ethylhexylglycerin, aloe barbadensis leaf juice, hydroxyacetophenone, glyceryl stearate, C30-45 alkyl cetearyl dimethicone crosspolymer, isohexadecane, acrylates/C10-30 alkyl acrylate crosspolymer, dicetyl phosphate, aminomethyl propanol, steareth-2, steareth-21, polysorbate 60, disodium EDTA, citric acid

PRINCIPAL DISPLAY PANEL

Cortizone 10
Itch Relief
Massaging Rollerball 1.5 FL OZ (44.3 mL)